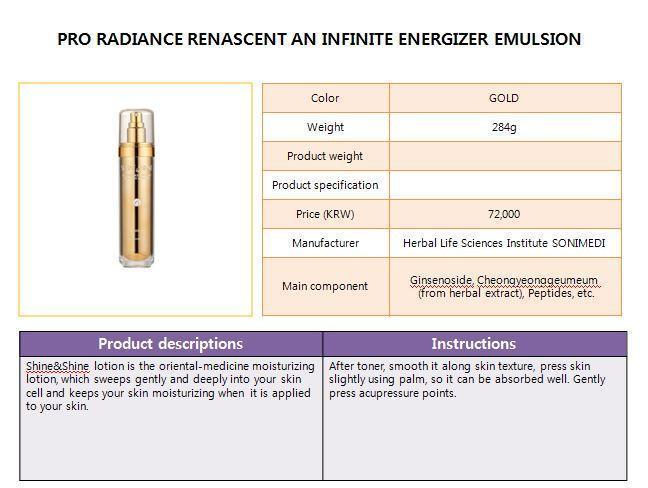 DRUG LABEL: PRO RADIANCE RENASCENT AN INFINITE ENERGIZER
NDC: 70067-1001 | Form: EMULSION
Manufacturer: Shine&Shine Co.,Ltd
Category: otc | Type: HUMAN OTC DRUG LABEL
Date: 20150903

ACTIVE INGREDIENTS: GLYCERIN 6 g/100 mL
INACTIVE INGREDIENTS: WATER; BUTYLENE GLYCOL

Drug Facts

ACTIVE INGREDIENT

glycerin

INACTIVE INGREDIENT

water, butylene glycol, allantoin etc.

PURPOSE

skin protectant

keep out of reach of the children

INDICATIONS AND USAGE

apply proper amount to the skin

WARNINGS

・Stop using the product when you have skin problems or the product disagrees with your skin
・Stop using the product immediately and consult a dermatologist if you have redness, swelling, itching or irritation on the skin while or after using the product.
・If the product gets into the eyes, don't rub but rinse with water.
・Don't place the product in any place where it will be subjected to extremely high or low temperatures or direct sunlight.

DOSAGE AND ADMINISTRATION

for external use only